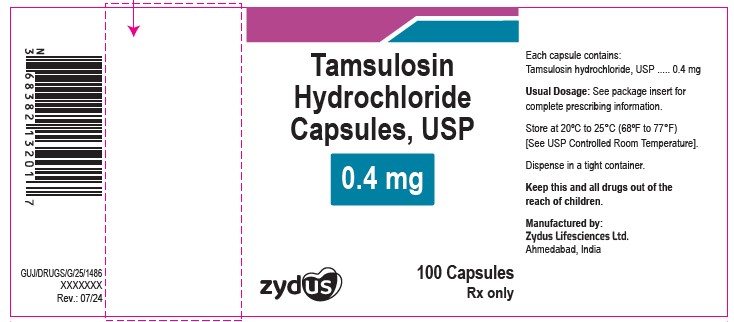 DRUG LABEL: Tamsulosin Hydrochloride
NDC: 65841-695 | Form: CAPSULE
Manufacturer: Zydus Lifesciences Limited
Category: prescription | Type: HUMAN PRESCRIPTION DRUG LABEL
Date: 20240812

ACTIVE INGREDIENTS: TAMSULOSIN HYDROCHLORIDE 0.4 mg/1 1
INACTIVE INGREDIENTS: D&C YELLOW NO. 10; FD&C BLUE NO. 1; FD&C RED NO. 40; FD&C YELLOW NO. 6; FERRIC OXIDE YELLOW; METHACRYLIC ACID; POLYSORBATE 80; GELATIN; TALC; TITANIUM DIOXIDE; TRIACETIN; FERROSOFERRIC OXIDE; CELLULOSE, MICROCRYSTALLINE

TAMSULOSIN HYDROCHLORIDE CAPSULES, USP

PACKAGE LABEL.PRINCIPAL DISPLAY PANEL

NDC 65841-695-01 in bottle of 100 Capsules

Tamsulosin Hydrochloride Capsules USP, 0.4 mg

Rx only

100 Capsules